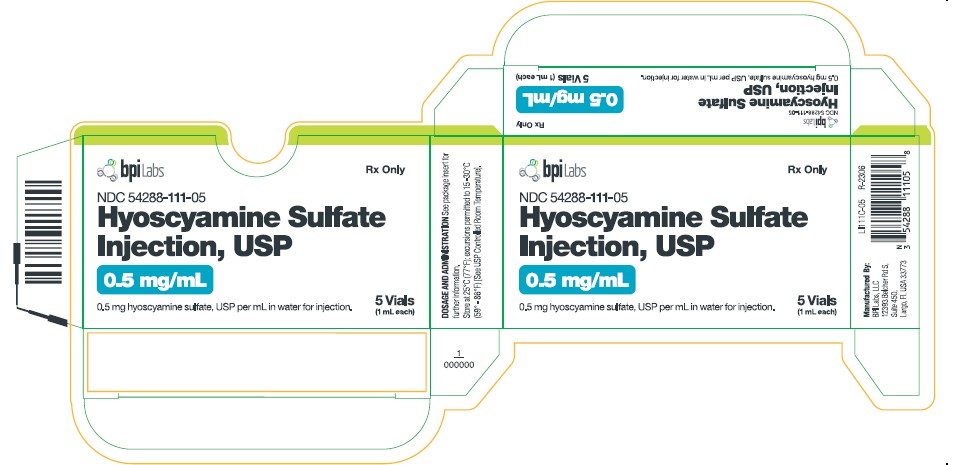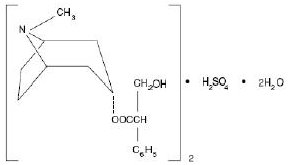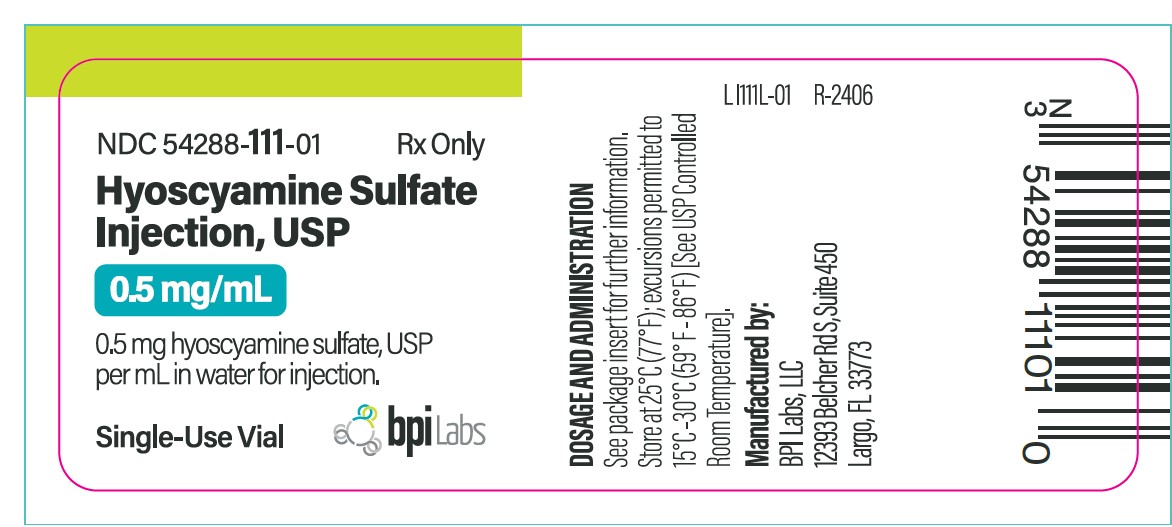 DRUG LABEL: HYOSCYAMINE SULFATE
NDC: 54288-111 | Form: INJECTION, SOLUTION
Manufacturer: BPI Labs LLC
Category: prescription | Type: HUMAN PRESCRIPTION DRUG LABEL
Date: 20251226

ACTIVE INGREDIENTS: HYOSCYAMINE SULFATE 0.5 mg/1 mL
INACTIVE INGREDIENTS: WATER

DESCRIPTION

Hyoscyamine sulfate injection, USP is a sterile solution containing 0.5 mg hyoscyamine sulfate per mL in water for injection.

Hyoscyamine sulfate Injection, USP is one of the principal anticholinergic/antispasmodic components of belladonna alkaloids. The empirical formula is (C 17H 23NO 3) 2•H 2SO 4•2H 20 and the molecular weight is 712.85. Chemically, it is benzeneacetic acid, α-(hydroxymethyl)-,8-methyl-8-azabicyclo [3.2.1.] oct-3-yl ester, [3(S)-endo]-, sulfate (2:1), dihydrate with the following structure:

The 1 mL vials contain as inactive ingredients: water for injection, pH is adjusted with hydrochloric acid when necessary.

CLINICAL PHARMACOLOGY

Hyoscyamine sulfate Injection, USP inhibits specifically the actions of acetylcholine on structures innervated by postganglionic cholinergic nerves and on smooth muscles that respond to acetylcholine but lack cholinergic innervation. These peripheral cholinergic receptors are present in the autonomic effector cells of the smooth muscle, cardiac muscle, the sinoatrial node, the atrioventricular node, and the exocrine glands. It is completely devoid of any action in the autonomic ganglia. Hyoscyamine sulfate Injection, USP inhibits gastrointestinal propulsive motility and decreases gastric acid secretion. Hyoscyamine sulfate Injection, USP also controls excessive pharyngeal, tracheal and bronchial secretions.

Hyoscyamine sulfate Injection, USP disappears rapidly from the blood and is distributed throughout the entire body. The half-life of Hyoscyamine sulfate Injection, USP is 31/2 hours. Hyoscyamine sulfate Injection, USP is partly hydrolyzed to tropic acid and tropine but the majority of the drug is excreted in the urine unchanged within the first 12 hours. Only traces of this drug are found in breast milk. Hyoscyamine sulfate Injection, USP passes the blood brain barrier and the placental barrier.

INDICATIONS AND USAGE

Hyoscyamine sulfate Injection, USP is effective as adjunctive therapy in the treatment of peptic ulcer. In acute episodes, Hyoscyamine sulfate Injection, USP can be used to control gastric secretion, visceral spasm and hypermotility in spastic colitis, spastic bladder, cystitis, pylorospasm, and associated abdominal cramps. For use as adjunctive therapy in the treatment of irritable bowel syndrome (irritable colon, spastic colon, mucous colitis) and functional gastrointestinal disorders. Also as adjunctive therapy in the treatment of neurogenic bladder and neurogenic bowel disturbances (including the splenic flexure syndrome and neurogenic colon). Parenterally administered Hyoscyamine sulfate Injection, USP is also effective in reducing gastrointestinal motility to facilitate diagnostic procedures such as endoscopy or hypotonic duodenography. Hyoscyamine sulfate Injection, USP may be used to reduce pain and hypersecretion in pancreatitis, in certain cases of partial heart block associated with vagal activity, and as an antidote for poisoning by anticholinesterase agents.

In Anesthesia:

Hyoscyamine sulfate Injection, USP is indicated as a pre-operative antimuscarinic to reduce salivary, tracheobronchial, and pharyngeal secretions, to reduce the volume and acidity of gastric secretions, and to block cardiac vagal inhibitory reflexes during induction of anesthesia and intubation. Hyoscyamine sulfate Injection, USP protects against the peripheral muscarinic effects such as bradycardia and excessive secretions produced by halogenated hydrocarbons and cholinergic agents such as physostigmine, neostigmine, and pyridostigmine given to reverse the actions of curariform agents.

In Urology:

Hyoscyamine sulfate Injection, USP may also be used intravenously to improve radiologic visibility of the kidneys. It is also indicated along with morphine or other narcotics in symptomatic relief of biliary and renal colic.

CONTRAINDICATIONS

Glaucoma; obstructive uropathy (for example, bladder neck obstruction due to prostatic hypertrophy); obstructive disease of the gastrointestinal tract (as in achalasia, pyloroduodenal stenosis); paralytic ileus, intestinal atony of elderly or debilitated patients; unstable cardiovascular status in acute hemorrhage; severe ulcerative colitis; toxic megacolon complicating ulcerative colitis; myasthenia gravis and myocardial ischemia.

WARNINGS

In the presence of high environmental temperature, heat prostration can occur with drug use (fever and heat stroke due to decreased sweating). Diarrhea may be an early symptom of incomplete intestinal obstruction, especially in patients with ileostomy or colostomy. In this instance, treatment with this drug would be inappropriate and possibly harmful. Like other anticholinergic agents, Hyoscyamine sulfate Injection, USP may produce drowsiness or blurred vision. In this event, the patient should be warned not to engage in activities requiring mental alertness such as operating a motor vehicle or other machinery or to perform hazardous work while taking this drug.

Psychosis has been reported in sensitive individuals given anticholinergic drugs. CNS signs and symptoms include confusion, disorientation, short term memory loss, hallucinations, dysarthria, ataxia, coma, euphoria, decreased anxiety, fatigue, insomnia, agitation and mannerisms, and inappropriate affect. These CNS signs and symptoms usually resolve within 12 to 48 hours after discontinuation of the drug.

PRECAUTIONS

General:

Use with caution in patients with: autonomic neuropathy, hyperthyroidism, coronary heart disease, congestive heart failure, cardiac arrhythmias, hypertension, and renal disease. Investigate any tachycardia before giving any anticholinergic drug since they may increase the heart rate. Use with caution in patients with hiatal hernia associated with reflux esophagitis.

Prolonged use of anticholinergics may decrease or inhibit salivary flow, thus contributing to the development of caries, periodontal disease, oral candidiasis, and discomfort.

Information for Patients:

Like other anticholinergic agents, Hyoscyamine sulfate Injection, USP may cause drowsiness, dizziness or blurred vision; patients should observe caution before driving, using machinery or performing other tasks requiring mental alertness.

Use of Hyoscyamine sulfate Injection, USP may decrease sweating resulting in heat prostration, fever or heat stroke; febrile patients or those who may be exposed to elevated environmental temperatures should use caution.

Drug Interactions:

Additive adverse effects resulting from cholinergic blockade may occur when Hyoscyamine sulfate Injection, USP is administered concomitantly with other anticholinergics, antimyasthenics, amantadine, cyclopropane, haloperidol, ketoconazole, metoclopramide, monoamine oxidase (MAO) inhibitors, opiod (narcotic) analgesics, phenothiazines, potassium chloride, tricyclic antidepressants and some antihistamines.

Carcinogenesis, Mutagenesis, Impairment of Fertility:

No long-term studies in animals have been performed to determine the carcinogenic, mutagenic or impairment of fertility potential of Hyoscyamine sulfate Injection, USP.

Pregnancy - Pregnancy Category C:

Animal reproduction studies have not been conducted with Hyoscyamine sulfate Injection, USP. It is also not known whether Hyoscyamine sulfate Injection, USP can cause fetal harm when administered to a pregnant woman or can affect reproduction capacity. Hyoscyamine sulfate injection should be given to a pregnant woman only if clearly needed.

Nursing Mothers:

Hyoscyamine sulfate Injection, USP is excreted in human milk. Caution should be exercised when Hyoscyamine sulfate Injection, USP is administered to a nursing woman.

Pediatric Use:

Infants and young children are especially susceptible to the toxic effects of anticholinergics. Close supervision is recommended for infants and children with spastic paralysis or brain damage since an increased response to anticholinergics has been reported in these patients and dosage adjustments are often required.

When anticholinergics are given to children where the environmental temperature is high, there is a risk of a rapid increase in body temperature because of these medications’ suppression of sweat gland activity.

A paradoxical reaction characterized by hyperexcitability may occur in children taking large doses of anticholinergics.

Geriatric Use:

Dose selection for an elderly patient should be cautious, usually starting at the low end of the dosing range, reflecting the greater frequency of decreased hepatic, renal, or cardiac function, and of concomitant disease or other drug therapy.

This drug is known to be substantially excreted by the kidney, and the risk of toxic reactions to this drug may be greater in patients with impaired renal function. Because elderly patients are more likely to have decreased renal function, care should be taken in dose selection, and it may be useful to monitor renal function.

Geriatric patients may respond to usual doses of anticholinergics with excitement, agitation, drowsiness or confusion.

Geriatric patients are especially susceptible to the anticholinergic side effects, such as constipation, dryness of mouth, and urinary retention (especially in males). Caution is also recommended when anticholinergics are given to geriatric patients, because of the danger of precipitating undiagnosed glaucoma.

Memory may become severely impaired in geriatric patients, especially those who already have memory problems, with the continued use of anticholinergics since these drugs block the actions of acetylcholine, which is responsible for many functions in the brain, including memory functions.

ADVERSE REACTIONS

Not all of the following adverse reactions have been reported with hyoscyamine sulfate. The following adverse reactions have been reported for pharmacologically similar drugs with anticholinergic/antispasmodic action.

Adverse reactions may include dryness of the mouth; urinary hesitancy and retention; blurred vision; tachycardia; palpitations; mydriasis; cycloplegia; increased ocular tension; loss of taste; headache; nervousness; drowsiness; weakness; dizziness; insomnia; nausea; vomiting; impotence; suppression of lactation; constipation; bloated feeling; allergic reactions or drug idiosyncrasies; urticaria and other dermal manifestations; ataxia; speech disturbance; some degree of mental confusion and/or excitement (especially in elderly persons); and decreased sweating.

To report SUSPECTED ADVERSE REACTIONS, contact BPI Labs, LLC, at (727-471-0850) or FDA at 1-800-FDA-1088 or www.fda.gov/medwatch.

OVERDOSAGE

The signs and symptoms of overdose are headache, nausea, vomiting, blurred vision, dilated pupils, hot dry skin, dizziness, dryness of the mouth, difficulty in swallowing, and CNS stimulation.

Measures to be taken are immediate lavage of the stomach and injection of physostigmine 0.5 to 2 mg intravenously and repeated as necessary up to a total of 5 mg. Fever may be treated symptomatically (tepid water sponge baths, hypothermic blanket). Excitement to a degree which demands attention may be managed with sodium thiopental 2% solution given slowly intravenously or chloral hydrate (100 to 200 mL of a 2% solution) by rectal infusion. In the event of progression of the curare-like effect to paralysis of the respiratory muscles, artificial respiration should be instituted and maintained until effective respiratory action returns.

In rats, the LD50 for hyoscyamine is 375 mg/kg. Hyoscyamine sulfate Injection, USP is dialyzable.

DOSAGE AND ADMINISTRATION

The dose may be administered subcutaneously, intramuscularly, or intravenously without dilution. As with all parenteral drug products, Hyoscyamine sulfate injection, USP should be inspected visually for particulate matter and discoloration prior to administration whenever solution and container permit.

Gastrointestinal Disorders:

The usual adult recommended dose is 0.5 to 1 mL (0.25 to 0.5 mg). Some patients may need only a single dose; others may require administration two, three, or four times a day at four hour intervals.

Diagnostic Procedures:

The usual adult recommended dose is 0.5 to 1 mL (0.25 to 0.5 mg) administered intravenously 5 to 10 minutes prior to the diagnostic procedure.

Anesthesia:

Adults and pediatric patients over 2 years of age:

As a pre-anesthetic medication, the recommended dose is 5 µg (0.005 mg) per kg of body weight. This dose is usually given thirty to sixty minutes prior to the anticipated time of induction of anesthesia or at the time the pre-anesthetic narcotic or sedatives are administered.

Hyoscyamine sulfate injection, USP may be used during surgery to reduce drug-induced bradycardia. It should be administered intravenously in increments of 0.25 mL and repeated as needed.

To achieve reversal of neuromuscular blockade, the recommended dose is 0.2 mg (0.4 mL) Hyoscyamine sulfate injection USP for every 1 mg neostigmine or the equivalent dose of physostigmine or pyridostigmine.

HOW SUPPLIED

Hyoscyamine sulfate injection USP (Hyoscyamine sulfate injection USP, 0.5 mg/mL), is available in 1 mL vials.

1 mL vials – Box of 5 NDC 54288-111-05

Store at 25°C (77°F); excursions permitted to 15° to 30°C (59° to 86°F) [See USP Controlled Room Temperature].

Also available as:

Product Dosage Strength Package Size NDC

Hyoscyamine sulfate injection, USP 0.5 mg/mL 5 Vials (1 mL Each) 54288-111-05

PRINCIPAL DISPLAY PANEL – 0.5 mg/mL

NDC 54288-111-01

Hyoscyamine sulfate Injection, USP

0.5 mg/mL

0.5 mg hyoscyamine sulfate, USP per mL in water for injection.

Single-Use Vial

Rx only

DOSAGE AND ADMINISTRATION:

See package insert for further information.

Store at 25°C (77°F);excursions permitted to 15° to 30°C (59° to 86°F)
[see USP Controlled Room Temperature].

Manufactured by:
BPI Labs LLC

12393 Belcher Rd S

Largo FL 33773

LI111L-01 R-2406

Carton: NDC 54288-111-05

Hyoscyamine sulfate Injection, USP

0.5 mg/mL

0.5 mg hyoscyamine sulfate, USP per mL in water for injection.

5 Vials (1 mL each)